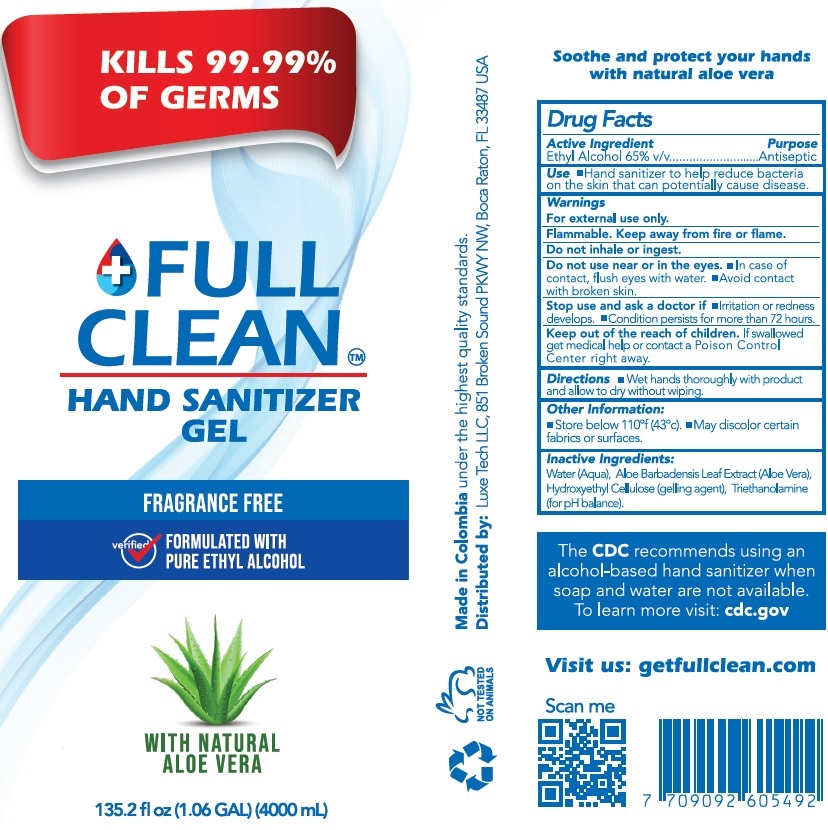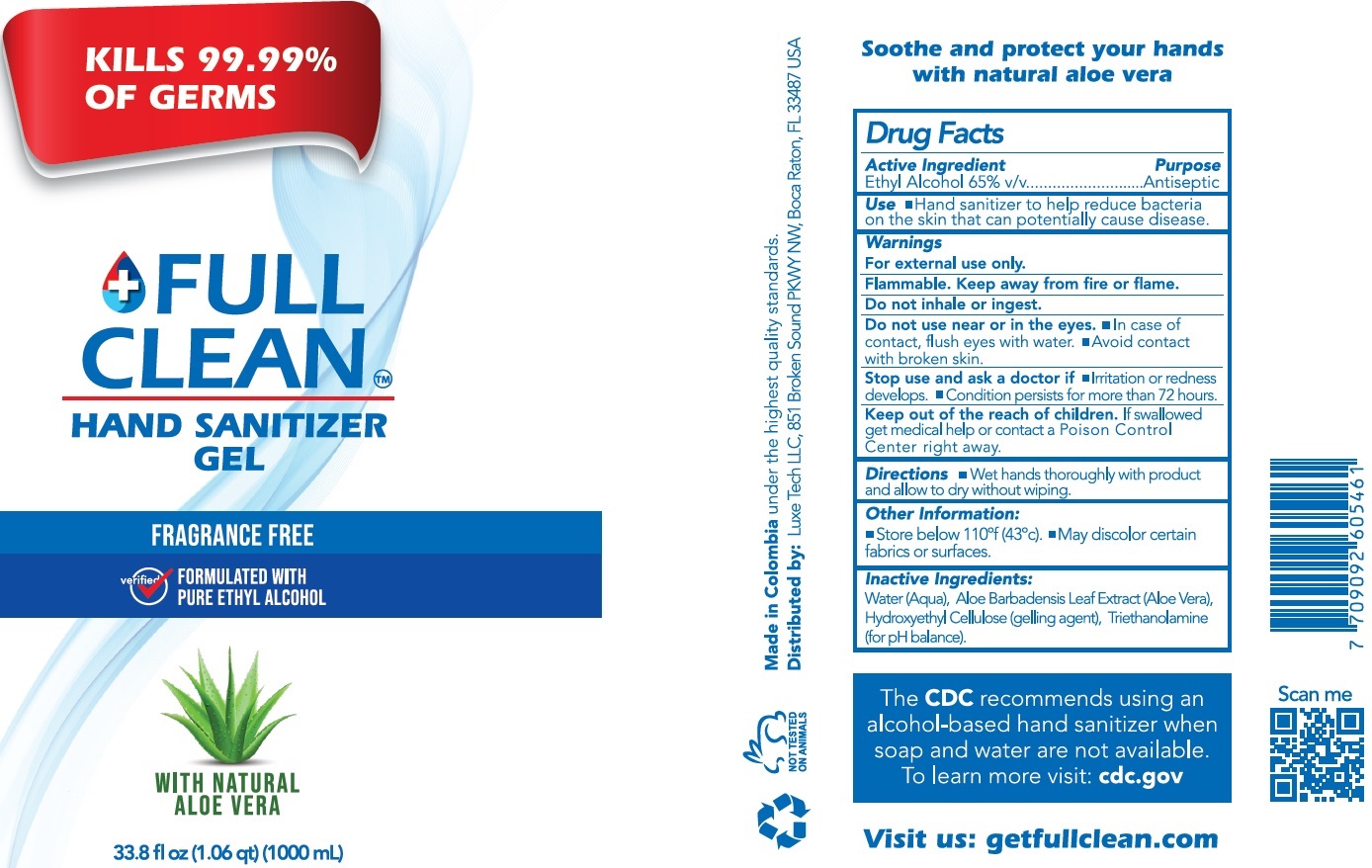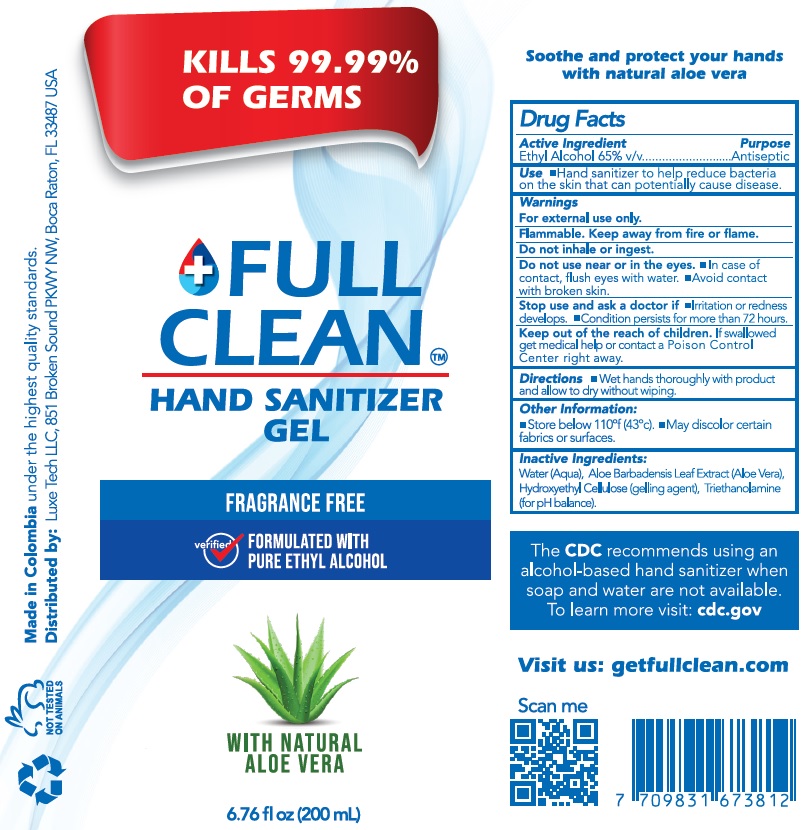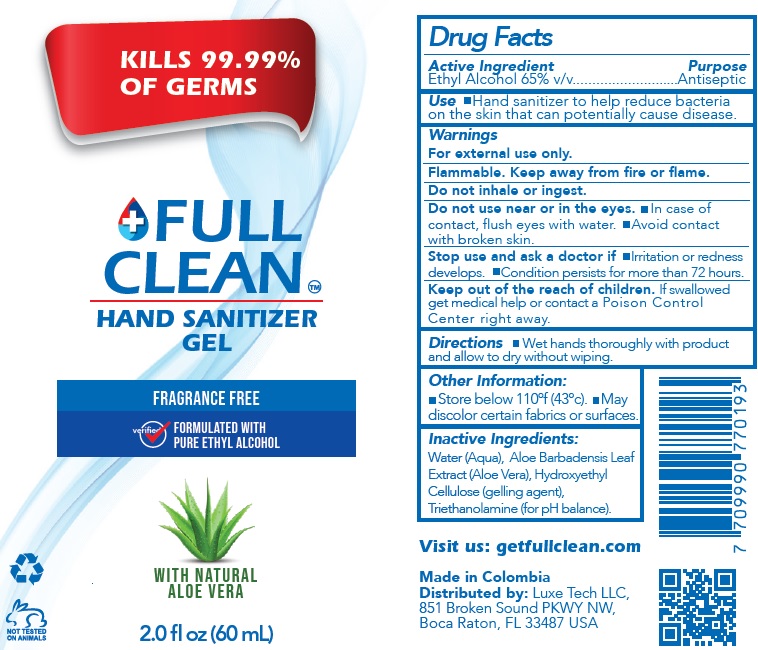 DRUG LABEL: Full Clean Hand Sanitizer
NDC: 81167-001 | Form: GEL
Manufacturer: Luxe Tech LLC
Category: otc | Type: HUMAN OTC DRUG LABEL
Date: 20210303

ACTIVE INGREDIENTS: ALCOHOL 0.65 mL/1 mL
INACTIVE INGREDIENTS: WATER; ALOE VERA LEAF; HYDROXYETHYL CELLULOSE, UNSPECIFIED; TROLAMINE

Full Clean Hand Sanitizer Gel

Active Ingredient

Ethyl Alcohol 65% v/v

Purpose

Antiseptic

Use

- Hand sanitizer to help reduce bacteria on the skin that can potentially cause disease.

Warnings

For external use only.
Flammable. Keep away from fire or flame.

Do not inhale or ingest.

Do not use

near or in the eyes.

- In case of contact, flush eyes with water. Avoid contact with broken skin.

Stop use and ask a doctor if

- Irritation or redness develops.
- Condition persists for more than 72 hours.

Keep out of the reach of children.

If swallowed get medical help or contact a Poison Control Center right away.

Directions

- Wet hands thoroughly with product and allow to dry without wiping.

Other Information:

- Store below 110ºf (43ºc).
- May discolor certain fabrics or surfaces.

Inactive Ingredients:

Water (Aqua), Aloe Barbadensis Leaf Extract (Aloe Vera), Hydroxyethyl Cellulose (gelling agent), Triethanolamine (for pH balance).